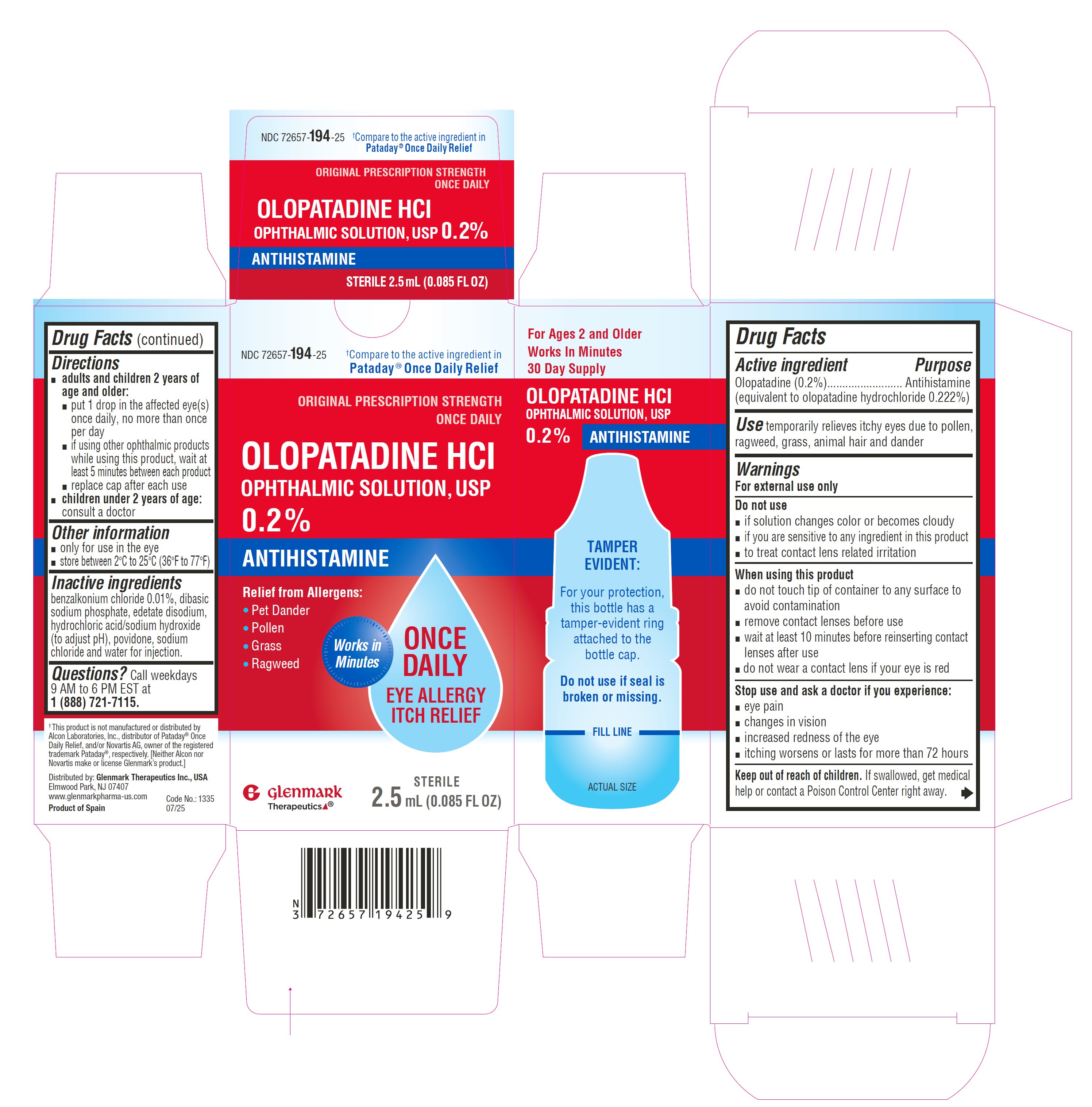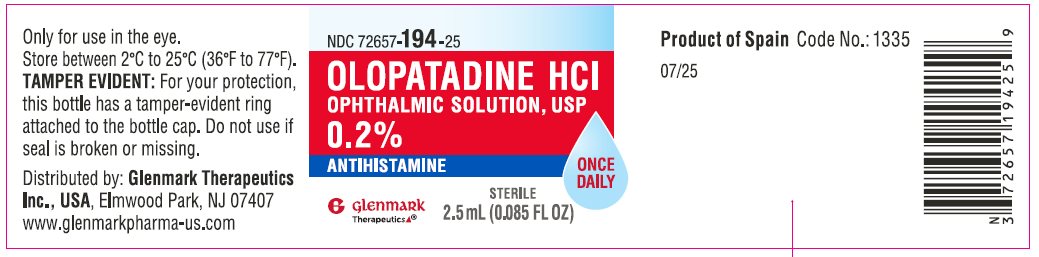 DRUG LABEL: OLOPATADINE HYDROCHLORIDE
NDC: 72657-194 | Form: SOLUTION
Manufacturer: GLENMARK THERAPEUTICS INC., USA
Category: otc | Type: HUMAN OTC DRUG LABEL
Date: 20260127

ACTIVE INGREDIENTS: OLOPATADINE HYDROCHLORIDE 2 mg/1 mL
INACTIVE INGREDIENTS: BENZALKONIUM CHLORIDE; EDETATE DISODIUM; HYDROCHLORIC ACID; POVIDONE K30; SODIUM CHLORIDE; SODIUM HYDROXIDE; SODIUM PHOSPHATE, DIBASIC, ANHYDROUS; WATER

Drug Facts

ACTIVE INGREDIENT

Active Ingredients | Purpose
Olopatadine 0.2% (equivalent to olopatadine hydrochloride 0.222%) | Antihistamine

INDICATIONS AND USAGE

Use temporarily relieves itchy eyes due to pollen, ragweed, grass, animal hair and dander

Warnings
For external use only

Do not use

- if solution changes color or becomes cloudy
- if you are sensitive to any ingredient in this product
- to treat contact lens related irritation

When using this product

- do not touch tip of container to any surface to avoid contamination
- remove contact lenses before use
- wait at least 10 minutes before reinserting contact lenses after use
- do not wear a contact lens if your eye is red

Stop use and ask a doctor if you experience:

- eye pain
- changes in vision
- increased redness of the eye
- itching worsens or lasts for more than 72 hours

Keep out of reach of children. If swallowed, get medical help or contact a Poison Control Center right away.

Directions

- adults and children 2 years of age and older:
  - put 1 drop in the affected eye(s) once daily, no more than once per day
  - if using other ophthalmic products while using this product, wait at least 5 minutes between each product
  - replace cap after each use
- children under 2 years of age: consult a doctor

Other information

- only for use in the eye
- store between 2°C to 25°C (36°F to 77°F)

Inactive ingredients

benzalkonium chloride 0.01%, dibasic sodium phosphate, edetate disodium, hydrochloric acid/sodium hydroxide (to adjust pH), povidone, sodium chloride and water for injection

Questions?

Call weekdays 9 AM to 6 PM EST at 1 (888) 721-7115.

Distributed by:

Glenmark Therapeutics Inc., USA

Elmwood Park, NJ 07407

Product of Spain

07/2025

PRINCIPAL DISPLAY PANEL

NDC 72657-194-25

Olopatadine HCl Ophthalmic Solution 0.2%

Antihistamine

Once Daily
STERILE

2.5 mL (0.085 FL OZ)

NDC: 72657-194-25

Original Prescription Strength
ONCE DAILY
Olopatadine HCl Ophthalmic Solution, USP 0.2%
Antihistamine
Eye Allergy Itch Relief

STERILE
2.5 mL (0.085 FL OZ)